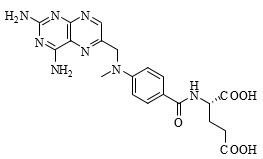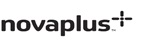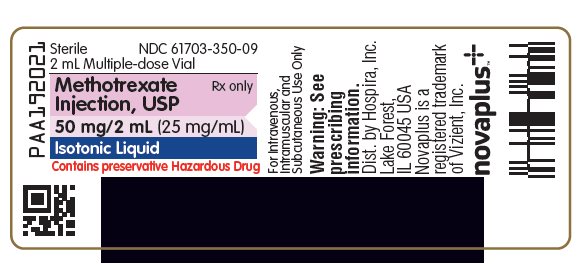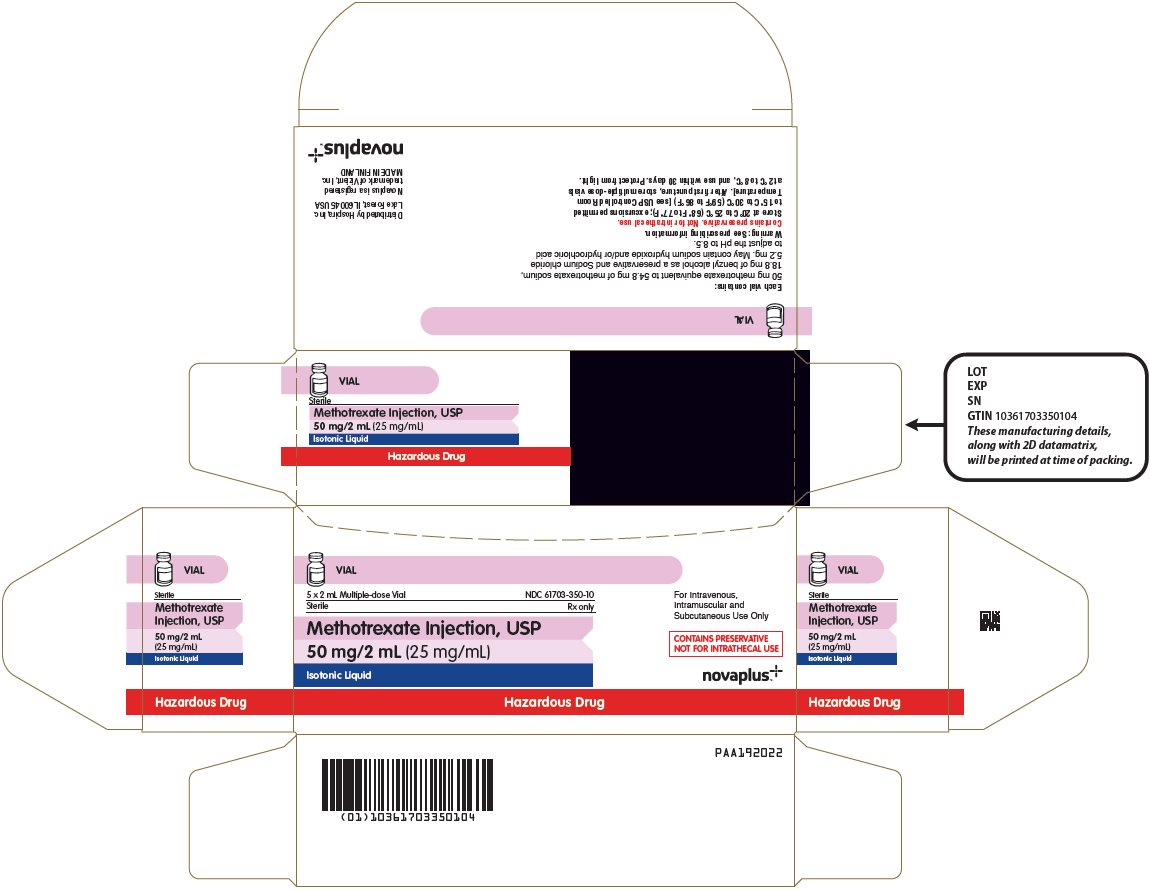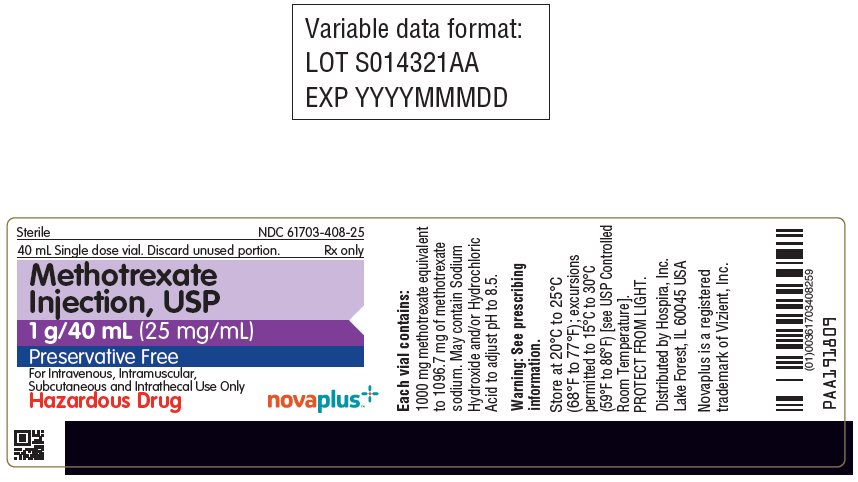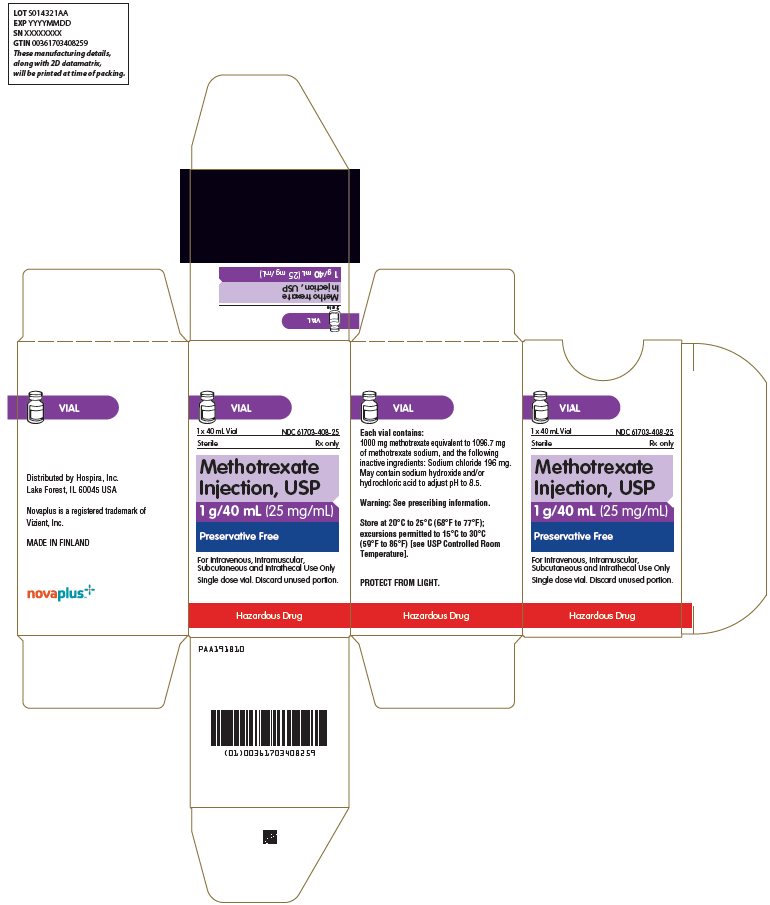 DRUG LABEL: Methotrexate
NDC: 61703-350 | Form: INJECTION, SOLUTION
Manufacturer: Hospira, Inc.
Category: prescription | Type: HUMAN PRESCRIPTION DRUG LABEL
Date: 20250822

ACTIVE INGREDIENTS: METHOTREXATE SODIUM 25 mg/1 mL
INACTIVE INGREDIENTS: BENZYL ALCOHOL; SODIUM CHLORIDE; WATER; SODIUM HYDROXIDE; HYDROCHLORIC ACID

HIGHLIGHTS OF PRESCRIBING INFORMATION

These highlights do not include all the information needed to use METHOTREXATE INJECTION safely and effectively. See full prescribing information for METHOTREXATE INJECTION.
METHOTREXATE injection, for intravenous, intramuscular, subcutaneous, or intrathecal use
Initial U.S. Approval: 1953

RECENT MAJOR CHANGES

Warnings and Precautions (5.11) | 05/2025

WARNING: EMBRYO-FETAL TOXICITY, HYPERSENSITIVITY REACTIONS, BENZYL ALCOHOL TOXICITY, and OTHER SERIOUS ADVERSE REACTIONS

See full prescribing information for complete boxed warning.

- Methotrexate Injection can cause embryo-fetal toxicity, including fetal death. Use in non-neoplastic diseases is contraindicated during pregnancy. Advise females and males of reproductive potential to use effective contraception during and after treatment with Methotrexate Injection. (4, 5.1, 8.1, 8.3)
- Methotrexate Injection is contraindicated in patients with a history of severe hypersensitivity reactions to methotrexate, including anaphylaxis. (4, 5.2)
- Formulations with benzyl alcohol can cause severe central nervous toxicity or metabolic acidosis. Use only preservative-free Methotrexate Injection for treatment of neonates or low birth weight infants, and for intrathecal use. Do not use benzyl alcohol-containing formulations for high-dose regimens unless immediate treatment is required and preservative-free formulations are not available. (2.1, 5.3)
- Other serious adverse reactions, including death, have been reported with methotrexate. Closely monitor for infections and adverse reactions of the bone marrow, kidneys, liver, nervous system, gastrointestinal tract, lungs, and skin. Withhold or discontinue Methotrexate Injection as appropriate. (5.4, 5.5, 5.6, 5.7, 5.8, 5.9, 5.10, 5.11)

1 INDICATIONS AND USAGE

Methotrexate Injection is a folate analog metabolic inhibitor indicated for:

- The following neoplastic diseases for the:
  - Treatment of adult and pediatric patients with acute lymphoblastic leukemia as part of a combination chemotherapy regimen. (1.1)
  - Prophylaxis and treatment of adult and pediatric patients with meningeal leukemia. (1.2)
  - Treatment of adult and pediatric patients with non-Hodgkin lymphoma. (1.3)
  - Treatment of adult and pediatric patients with osteosarcoma as part of a combination chemotherapy regimen. (1.4)
  - Treatment of adults with breast cancer as part of a combination chemotherapy regimen. (1.5)
  - Treatment of adults with squamous cell carcinoma of the head and neck as a single agent. (1.6)
  - Treatment of adults with gestational trophoblastic neoplasia as part of a combination chemotherapy regimen. (1.7)
- Treatment of adults with rheumatoid arthritis (RA). (1.8)
- Treatment of pediatric patients with polyarticular juvenile idiopathic arthritis (pJIA). (1.9)
- Treatment of adults with severe psoriasis. (1.10)

2 DOSAGE AND ADMINISTRATION

- Verify pregnancy status in females of reproductive potential before starting Methotrexate Injection. (2.1, 4, 5.1)
- Neoplastic diseases: Refer to the prescribing information for disease specific dosing recommendations. Follow guidelines for high-dose regimens. (2.2, 2.3, 2.4, 2.5, 2.6, 2.7, 2.8, 2.9)
- RA: Recommended starting dosage of 7.5 mg once weekly intramuscularly; adjust dose to achieve an optimal response. (2.10)
- pJIA: Recommended starting dosage of 10 mg/m^2 once weekly subcutaneously or intramuscularly; adjust dose to achieve an optimal response. (2.11)
- Psoriasis: Recommended dosage of 10 mg to 25 mg once weekly intramuscularly or intravenously; adjust dose to achieve optimal response. Once achieved, reduce to lowest possible dosage. (2.12)

3 DOSAGE FORMS AND STRENGTHS

Injection: (3)

- With preservative (multiple-dose vials): 50 mg/2 mL (25 mg/mL)
- Preservative-free (single-dose vials): 1 g/40 mL (25 mg/mL)

4 CONTRAINDICATIONS

- History of severe hypersensitivity to methotrexate. (4)
- Pregnancy: in patients with non-neoplastic diseases. (4)

5 WARNINGS AND PRECAUTIONS

- Secondary malignancies can occur. (5.13)
- Tumor lysis syndrome can occur in patients with rapidly growing tumors. (5.14)
- Immunizations and Risks associated with Live Vaccines: Immunizations may be ineffective. Live vaccines are not recommended due to risk of disseminated infection. (5.15)
- Infertility: Can cause impairment of fertility, oligospermia, and menstrual dysfunction. (5.16, 8.3)

6 ADVERSE REACTIONS

Common adverse reactions include ulcerative stomatitis, leukopenia, nausea, and abdominal distress. (6.1)

To report SUSPECTED ADVERSE REACTIONS, contact Pfizer Inc. at 1-800-438-1985 or FDA at 1-800-FDA-1088 or www.fda.gov/medwatch.

7 DRUG INTERACTIONS

Refer to full prescribing information for drug interactions with Methotrexate Injection. (7)

8 USE IN SPECIFIC POPULATIONS

- Lactation: Advise not to breastfeed. (8.2)
- Pediatric use: Intermediate-dose methotrexate can cause serious neurotoxicity in patients with acute lymphoblastic leukemia. (8.4)

FULL PRESCRIBING INFORMATION

WARNING: EMBRYO-FETAL TOXICITY, HYPERSENSITIVITY REACTIONS, BENZYL ALCOHOL TOXICITY, and OTHER SERIOUS ADVERSE REACTIONS

- Methotrexate Injection can cause embryo-fetal toxicity, including fetal death. For non-neoplastic diseases, Methotrexate Injection is contraindicated in pregnancy. Advise females and males of reproductive potential to use effective contraception [see Contraindications (4), Warnings and Precautions (5.1), and Use in Specific Populations (8.1, 8.3)].
- Methotrexate Injection is contraindicated in patients with a history of severe hypersensitivity reactions to methotrexate, including anaphylaxis [see Contraindications (4) and Warnings and Precautions (5.2)].
- Formulations with benzyl alcohol can cause severe central nervous toxicity or metabolic acidosis. Use only preservative-free Methotrexate Injection for treatment of neonates or low birth weight infants and for intrathecal use. Do not use benzyl alcohol-containing formulations for high-dose regimens unless immediate treatment is required and preservative-free formulations are not available [see Dosage and Administration (2.1) and Warnings and Precautions (5.3)].
- Other serious adverse reactions, including death, have been reported with methotrexate. Closely monitor for infections and adverse reactions of the bone marrow, kidneys, liver, nervous system, gastrointestinal tract, lungs, and skin. Withhold or discontinue Methotrexate Injection as appropriate [see Warnings and Precautions (5.4, 5.5, 5.6, 5.7, 5.8, 5.9, 5.10, 5.11)].

1 INDICATIONS AND USAGE

1.1 Acute Lymphoblastic Leukemia

Methotrexate Injection is indicated for the treatment of adult and pediatric patients with acute lymphoblastic leukemia (ALL) as part of a combination chemotherapy regimen.

1.2 Meningeal Leukemia: Prophylaxis and Treatment

Methotrexate Injection is indicated for the prophylaxis and treatment of meningeal leukemia in adult and pediatric patients.

1.3 Non-Hodgkin Lymphoma

Methotrexate Injection is indicated for the treatment of adults and pediatric patients with non-Hodgkin lymphoma.

1.4 Osteosarcoma

Methotrexate Injection is indicated for the treatment of adults and pediatric patients with osteosarcoma as part of a combination chemotherapy regimen.

1.5 Breast Cancer

Methotrexate Injection is indicated for the treatment of adults with breast cancer as part of a combination chemotherapy regimen.

1.6 Squamous Cell Carcinoma of the Head and Neck

Methotrexate Injection is indicated for the treatment of adults with squamous cell carcinoma of the head and neck as a single agent.

1.7 Gestational Trophoblastic Neoplasia

Methotrexate Injection is indicated for the treatment of adults with gestational trophoblastic neoplasia (GTN) as part of a combination chemotherapy regimen.

1.8 Rheumatoid Arthritis

Methotrexate Injection is indicated for the treatment of adults with rheumatoid arthritis (RA).

1.9 Polyarticular Juvenile Idiopathic Arthritis

Methotrexate Injection is indicated for the treatment of pediatric patients with polyarticular Juvenile Idiopathic Arthritis (pJIA).

1.10 Psoriasis

Methotrexate Injection is indicated for the treatment of adults with severe psoriasis.

2 DOSAGE AND ADMINISTRATION

2.1 Important Dosage and Safety Information

- Use only preservative-free Methotrexate Injection for treatment of neonates or low birth weight infants and for intrathecal use. Do not use benzyl alcohol-containing formulations for high-dose regimens unless immediate treatment is required and preservative-free formulations are not available [see Warnings and Precautions (5.3) and Use in Specific Populations (8.4)].
- Verify pregnancy status in females of reproductive potential before starting Methotrexate Injection [see Contraindications (4) and Warnings and Precautions (5.1)].
- For patients switching between a methotrexate product administered orally and Methotrexate Injection, consider potential differences in bioavailability.

2.2 Recommended Monitoring and Concomitant Therapies for Intermediate- and High-Dose Regimens

To decrease the risk of severe adverse reactions [see Warnings and Precautions (5)]:

- Administer leucovorin rescue in patients receiving Methotrexate Injection doses of 500 mg/m^2 or greater (e.g., high-dose).
- Consider leucovorin rescue for patients receiving Methotrexate Injection doses between 100 mg/m^2 to less than 500 mg/m^2 (e.g., intermediate-dose).

Refer to the leucovorin prescribing information for additional information.

- For high-dose Methotrexate Injection regimens, follow the supportive care and monitoring instructions below. Also consider for patients receiving intermediate-dose Methotrexate Injection regimens.
  - Monitor serum creatinine, electrolytes, at baseline and at least daily during therapy
  - Administer intravenous fluids starting before the first dose and continuing throughout treatment to maintain adequate hydration and urine output
  - Alkalinize urine starting before the first dose and continuing throughout treatment to maintain a urinary pH of 7 or higher
  - Monitor methotrexate concentrations at least daily and adjust hydration and leucovorin dosing as needed
- Administer glucarpidase in patients who have toxic plasma methotrexate concentrations (>1 micromole per liter) and delayed methotrexate clearance due to impaired renal function (refer to the glucarpidase prescribing information for additional information).

2.3 Recommended Dosage for Acute Lymphoblastic Leukemia

Methotrexate Injection is used as part of a multi-drug regimen. The recommended dosage varies from 10 to 5000 mg/m^2 intravenously. For high-dose Methotrexate Injection regimens, use leucovorin rescue in accordance with high-dose methotrexate regimen guidelines [see Dosage and Administration (2.2)]. Lower doses (e.g., 20 to 30 mg/m^2 per week) may be used intramuscularly. Individualize the dose and schedule of Methotrexate Injection based on disease state, patient risk category, concurrent drugs used, phase of treatment, and response to treatment.

2.4 Recommended Dosage for Meningeal Leukemia: Prophylaxis and Treatment

Use only preservative-free Methotrexate Injection for intrathecal use.

Prior to administration, dilute preservative-free Methotrexate Injection to a concentration of 1 mg/mL in preservative-free 0.9% Sodium Chloride Injection, USP.

The recommended intrathecal dose of Methotrexate Injection (preservative-free) is based on age:

- less than 1 year: 6 mg
- 1 to less than 2 years: 8 mg
- 2 to less than 3 years: 10 mg
- 3 to less than 9 years: 12 mg
- greater than or equal to 9 years: 12 to15 mg

For treatment of meningeal leukemia, intrathecal methotrexate may be given at intervals of 2 or more days up to twice weekly; however, administration at intervals of less than 1 week may result in increased subacute toxicity. For meningeal leukemia prophylaxis, Methotrexate Injection is administered no more than once weekly.

For patients with Down Syndrome, administer leucovorin rescue with intrathecal Methotrexate Injection.

2.5 Recommended Dosage for Non-Hodgkin Lymphoma

The recommended dosage of Methotrexate Injection varies. When used in combination, recommended dosages range from 10 mg/m^2 to 8000 mg/m^2 intravenously. When used as a single agent, recommended dosages include 8000 mg/m^2 intravenously for central nervous system-directed therapy or 5 to 75 mg intravenously for cutaneous forms of non-Hodgkin lymphoma.

As part of a combination chemotherapy regimen, a recommended dosage of Methotrexate Injection is 1000 mg/m^2 or 3000 mg/m^2 as an intravenous infusion over 24 hours followed by leucovorin rescue in accordance with high-dose methotrexate regimen guidelines [see Dosage and Administration (2.2)].

For central nervous system-directed therapy, a recommended dosage of Methotrexate Injection is 8000 mg/m^2 as an intravenous infusion over 4 hours as a single agent or in combination with immunochemotherapy at doses ranging from 3000 mg/m^2 to 8000 mg/m^2 followed by leucovorin rescue in accordance with high-dose methotrexate regimen guidelines [see Dosage and Administration (2.2)].

For intrathecal Methotrexate Injection (preservative-free), the recommended dose is based on age [see Dosage and Administration (2.4)]. The frequency of administration varies based on whether it is being used for treatment or prophylaxis, and other factors.

2.6 Recommended Dosage for Osteosarcoma

The recommended dosage of Methotrexate Injection is typically 12 g/m^2 (maximum 20 g/dose) as an intravenous infusion over 4 hours administered as a component of a combination chemotherapy regimen. Administer leucovorin rescue in accordance with high-dose methotrexate regimen guidelines [see Dosage and Administration (2.2)]. Subsequent doses may need to be adjusted based on observed peak serum methotrexate concentrations. Dosage and schedule may vary based upon factors such as patient comorbidities, disease state, and prior treatments.

2.7 Recommended Dosage for Breast Cancer

A recommended dosage of Methotrexate Injection is 40 mg/m^2 intravenously as a component of a cyclophosphamide- and fluorouracil-based multi-drug regimen.

2.8 Recommended Dosage for Squamous Cell Carcinoma of Head and Neck

The recommended dosage of Methotrexate Injection ranges from 40 to 60 mg/m^2 intravenously once weekly.

2.9 Recommended Dosage for Gestational Trophoblastic Neoplasia

For patients with low-risk gestational trophoblastic neoplasia (GTN) a recommended dosage for Methotrexate Injection is 30 mg/m^2 to 200 mg/m^2 or 0.4 mg/kg to1 mg/kg intravenously or intramuscularly.

For patients with high-risk GTN, a recommended dosage for Methotrexate Injection is 300 mg/m^2 over 12 hours as an intravenous infusion as a component of a multi-drug regimen.

2.10 Recommended Dosage for Rheumatoid Arthritis

The recommended starting dosage of Methotrexate Injection is 7.5 mg once weekly, administered intramuscularly with escalation to achieve optimal response. Dosages of more than 20 mg once weekly result in an increased risk of serious adverse reactions, including myelosuppression.

When responses are observed, the majority occurred between 3 and 6 weeks from initiation of treatment; however, responses have occurred up to 12 weeks after treatment initiation.

Administer folic acid or folinic acid to reduce the risk of methotrexate adverse reactions [see Warnings and Precautions (5.12)].

2.11 Recommended Dosage for Polyarticular Juvenile Idiopathic Arthritis

The recommended starting dosage of Methotrexate Injection is 10 mg/m^2 once weekly administered subcutaneously or intramuscularly, with escalation to achieve optimal response. Dosages over 30 mg/m^2 per week may result in an increased risk of serious adverse reactions, including myelosuppression. When responses are observed, the majority occurred between 3 and 6 weeks from initiation of treatment; however, responses have occurred up to 12 weeks after treatment initiation.

Administer folic acid or folinic acid to reduce the risk of methotrexate adverse reactions [see Warnings and Precautions (5.12)].

2.12 Recommended Dosage for Psoriasis

The recommended dosage of Methotrexate Injection is 10 mg to 25 mg intramuscularly or intravenously once weekly until adequate response is achieved.

Adjust the dose gradually to achieve optimal clinical response; do not exceed 25 mg per week. Once optimal clinical response has been achieved, reduce the dosage to the lowest possible dosing regimen.

Administer folic acid or folinic acid to reduce the risk of methotrexate adverse reactions [see Warnings and Precautions (5.12)].

2.13 Dosage Modifications for Adverse Reactions

Discontinue Methotrexate Injection for:

- Anaphylaxis or other severe hypersensitivity reactions [see Warnings and Precautions (5.2)]
- Lymphoproliferative disease [see Warnings and Precautions (5.13)]

Withhold, dose reduce or discontinue Methotrexate Injection as appropriate for:

- Myelosuppression [see Warnings and Precautions (5.4)]

Withhold or discontinue Methotrexate Injection as appropriate for:

- Serious infections [see Warnings and Precautions (5.5)]
- Renal toxicity [see Warnings and Precautions (5.6)]
- Hepatotoxicity [see Warnings and Precautions (5.7)]
- Neurotoxicity [see Warnings and Precautions (5.8)]
- Gastrointestinal toxicity [see Warnings and Precautions (5.9)]
- Pulmonary toxicity [see Warnings and Precautions (5.10)]
- Dermatologic reactions [see Warnings and Precautions (5.11)]

2.14 Administration and Handling Information

Methotrexate Injection is a hazardous drug. Follow applicable special handling and disposable procedures.^1

With Preservative (Multiple-Dose Vial)

- Methotrexate Injection formulation containing benzyl alcohol as a preservative may be administered by intramuscular, intravenous, or subcutaneous injection [see Dosage and Administration (2.1)]. Methotrexate Injection with preservative may be further diluted with 0.9% Sodium Chloride Injection, USP. Diluted product should be used within 4 hours when stored at room temperature (20°C to 25°C) or 24 hours under refrigeration (2°C to 8°C).
- Visually inspect product for particulate matter and discoloration prior to administration. Discard if particulate matter or discoloration is observed.

Preservative-Free (Single-Dose Vial)

Methotrexate Injection preservative-free may be administered by intramuscular, intravenous, subcutaneous, or intrathecal injection.

- Use only preservative-free Methotrexate Injection for treatment of neonates or low birth weight infants and for intrathecal use [see Warning and Precautions (5.3) and Use in Specific Populations (8.4)].
- Use preservative-free Methotrexate Injection for high-dose regimens unless immediate treatment is required, and preservative-free formulations are not available [see Warning and Precautions (5.3) and Use in Specific Populations (8.4)].
- Preservative-free Methotrexate Injection may be further diluted before use with preservative‑free 0.9% Sodium Chloride Injection, USP. Diluted product should be used within 4 hours when stored at room temperature (20°C to 25°C) or 24 hours when stored under refrigeration (2°C to 8°C).
- Visually inspect for particulate matter and discoloration prior to administration. Discard if particulate matter or discoloration is observed.

3 DOSAGE FORMS AND STRENGTHS

Injection: Methotrexate Injection is a clear, yellow solution and is supplied in single-dose vials (preservative-free) and multiple-dose vials (with preservative) in the following strengths:

With Preservative (Multiple-Dose Vial)

- 50 mg/2 mL (25 mg/mL)

Preservative-Free (Single-Dose Vial)

- 1 g/40 mL (25 mg/mL)

4 CONTRAINDICATIONS

Methotrexate Injection is contraindicated in:

- Patients with history of severe hypersensitivity to methotrexate [see Warnings and Precautions (5.2)].
- Pregnancy in patients with non-neoplastic diseases [see Warnings and Precautions (5.1) and Use in Specific Populations (8.1)].

5 WARNINGS AND PRECAUTIONS

5.1 Embryo-Fetal Toxicity

Based on published reports and its mechanism of action, methotrexate can cause embryo-fetal toxicity, including fetal death when administered to a pregnant woman.

Methotrexate Injection is contraindicated for use in pregnant women with non-neoplastic diseases. Advise pregnant women with neoplastic diseases of the potential risk to a fetus. The preservative benzyl alcohol can cross the placenta; when possible, use the preservative-free formulation when Methotrexate Injection is needed during pregnancy to treat a neoplastic disease [see Warnings and Precautions (5.3)].

Advise females of reproductive potential to use effective contraception during Methotrexate Injection treatment and for 6 months after the last dose. Advise males with female partners of reproductive potential to use effective contraception during Methotrexate Injection treatment and for 3 months after the last dose [see Contraindications (4) and Use in Specific Populations (8.1, 8.3, 8.4)].

5.2 Hypersensitivity Reactions

Hypersensitivity reactions, including anaphylaxis, can occur with methotrexate [see Adverse Reactions (6.1)]. If signs or symptoms of anaphylaxis or any other serious hypersensitivity reaction occurs, immediately discontinue Methotrexate Injection and institute appropriate therapy [see Contraindications (4)].

5.3 Risks of Serious Adverse Reactions due to Benzyl Alcohol-Preservative

Formulations with benzyl alcohol can cause severe central nervous toxicity or metabolic acidosis, if used in neonates or low birth weight infants, intrathecally, or in high-dose regimens. Use only preservative-free Methotrexate Injection for treatment of neonates or low birth weight infants and for intrathecal use. Do not use benzyl alcohol-containing formulations for high-dose regimens unless immediate treatment is required, and preservative-free formulations are not available. The preservative benzyl alcohol can cross the placenta; when possible, use the preservative-free formulation when Methotrexate Injection is needed during pregnancy to treat a neoplastic disease [see Use in Specific Populations (8.1)].

Serious and Fatal Adverse Reactions Including Gasping Syndrome in Neonates and Low Birth Weight Infants

Serious and fatal adverse reactions including "gasping syndrome" can occur in neonates and low birth weight infants treated with drugs containing benzyl alcohol, including Methotrexate Injection with preservative. The "gasping syndrome" is characterized by central nervous system (CNS) depression, metabolic acidosis, and gasping respirations.

When prescribing in infants (non-neonate, non-low birth weight), if a preservative-free formulation of Methotrexate Injection is not available and use of a benzyl alcohol-containing formulation is necessary, consider the combined daily metabolic load of benzyl alcohol from all sources including Methotrexate Injection (Methotrexate Injection contains 9.4 mg of benzyl alcohol per mL) and other drugs containing benzyl alcohol. The minimum amount of benzyl alcohol at which serious adverse reactions may occur is not known [see Use in Specific Populations (8.4)].

Neurotoxicity Due to Intrathecal Administration

Serious neurotoxicity can occur following the intrathecal administration of Methotrexate Injection containing the preservative benzyl alcohol.

Metabolic Acidosis with High-Dose Therapy

Severe metabolic acidosis can occur with Methotrexate Injection that contains the preservative benzyl alcohol.

5.4 Myelosuppression

Methotrexate suppresses hematopoiesis and can cause severe and life-threatening pancytopenia, anemia, aplastic anemia, leukopenia, neutropenia, and thrombocytopenia [see Adverse Reactions (6.1)].

Obtain blood counts at baseline and periodically during treatment. Monitor patients for possible clinical complications of myelosuppression. Provide supportive care and withhold, reduce dose, or discontinue Methotrexate Injection as needed.

5.5 Serious Infections

Patients treated with methotrexate are at increased risk for developing life-threatening or fatal bacterial, fungal, or viral infections including opportunistic infections such as Pneumocystis jiroveci pneumonia, invasive fungal infections, hepatitis B reactivation, tuberculosis primary infection or reactivation, and disseminated Herpes zoster and cytomegalovirus infections.

Closely monitor patients for the development of signs and symptoms of infection during and after treatment with Methotrexate Injection. Withhold or discontinue Methotrexate Injection in patients who develop serious infections.

5.6 Renal Toxicity

Methotrexate can cause renal toxicity including irreversible acute renal failure. Monitor renal function and withhold or discontinue Methotrexate Injection as needed for severe renal toxicity.

For patients receiving high-dose regimens, follow recommendations to decrease the risk of renal injury and mitigate renal toxicity [see Dosage and Administration (2.2)].

Patients with impaired renal function are at increased risk for methotrexate toxicity [see Use in Specific Populations (8.6)].

Consider administration of glucarpidase in patients with toxic plasma methotrexate concentrations (>1 micromole per liter) and delayed clearance due to impaired renal function. [see Dosage and Administration (2.2)].

5.7 Hepatotoxicity

Methotrexate can cause severe and potentially irreversible hepatotoxicity including fibrosis, cirrhosis, and fatal liver failure [see Adverse Reactions (6.1, 6.2)].

In patients with psoriasis, fibrosis or cirrhosis may occur in the absence of symptoms or abnormal liver function tests. In patients with psoriasis, the risk of hepatotoxicity appears to increase with total cumulative dose and generally occurs after receipt of a total cumulative dose of 1.5 g or more.

The safety of Methotrexate Injection in patients with liver disease is unknown. Avoid use of Methotrexate Injection in patients with chronic liver disease, unless benefits clearly outweigh the risks. The risk of hepatotoxicity is increased with heavy alcohol consumption.

Assess liver function prior to initiating Methotrexate Injection and monitor liver function tests during treatment. Withhold or discontinue Methotrexate Injection as appropriate.

5.8 Neurotoxicity

Methotrexate can cause severe acute and chronic neurotoxicity which can be progressive, irreversible, and fatal. Serious neurotoxicity, including generalized and focal seizures, have occurred in pediatric patients [see Use in Specific Populations (8.4)]. Monitor patients for signs of neurotoxicity and withhold or discontinue Methotrexate Injection when appropriate.

Leukoencephalopathy

Leukoencephalopathy can occur with intermediate and high-dose intravenous regimens, intrathecal methotrexate, and low-dose methotrexate therapy. The risk of leukoencephalopathy is increased with prior cranial radiation.

Transient Acute Neurologic Syndrome

A transient acute stroke-like syndrome can occur with high-dose methotrexate. Clinical manifestations include confusion, hemiparesis, transient blindness, seizures, and coma.

Neurologic Adverse Reactions Associated with Intrathecal Administration

Intrathecal methotrexate can cause the following additional neurologic adverse reactions:

- Acute chemical arachnoiditis manifested by symptoms such as headache, back pain, nuchal rigidity, and fever.
- Subacute myelopathy characterized by paraparesis or paraplegia.

Avoid the intrathecal use of Methotrexate Injection that contains the preservative benzyl alcohol because of the risk of serious neurotoxicity [see Warnings and Precautions (5.3)].

5.9 Gastrointestinal Toxicity

Methotrexate can cause diarrhea, vomiting, stomatitis, hemorrhagic enteritis and fatal intestinal perforation [see Adverse Reactions (6.1)]. Patients with peptic ulcer disease or ulcerative colitis are at a greater risk of developing severe gastrointestinal adverse reactions.

Withhold or discontinue Methotrexate Injection for severe gastrointestinal toxicity, and institute appropriate supportive care as needed.

5.10 Pulmonary Toxicity

Methotrexate-induced pulmonary toxicity including acute or chronic interstitial pneumonitis and irreversible or fatal cases can occur at all dose levels. Monitor patients for signs of pulmonary toxicity and withhold or discontinue Methotrexate Injection as appropriate.

5.11 Dermatologic Reactions

Severe, including fatal, dermatologic reactions, such as toxic epidermal necrolysis, Stevens-Johnson syndrome, exfoliative dermatitis, skin necrosis, and erythema multiforme, can occur with methotrexate [see Adverse Reactions (6.1, 6.2)].

Psoriasis may be aggravated by concomitant exposure to ultraviolet radiation.

Methotrexate can cause radiation recall, photodermatitis (sunburn) reactivation, photosensitivity, and severe sunburn reactions. Advise patients to limit sun exposure while taking Methotrexate Injection. Advise patients when outdoors to wear a hat and protective clothing and use a broad-spectrum Ultraviolet A (UVA)/Ultraviolet B (UVB) sunscreen and lip balm (SPF ≥30) to help protect against sunburn.

Monitor patients for signs of dermatologic toxicity and withhold or permanently discontinue Methotrexate Injection for severe dermatologic adverse reactions.

5.12 Folic Acid Supplementation

Neoplastic Diseases

Products containing folic acid or its derivatives may decrease the clinical effectiveness of methotrexate. Avoid use of products containing folic acid or folinic acid unless clinically indicated [see Drug Interactions (7.1)].

Non-neoplastic Diseases

Folate deficiency may increase methotrexate adverse reactions. Administer folic acid or folinic acid to patients with rheumatoid arthritis, pJIA, and psoriasis [see Dosage and Administration (2.10, 2.11, 2.12)].

5.13 Secondary Malignancies

Secondary malignancies can occur at all dose levels of methotrexate. In some cases, lymphoproliferative disease that occurred during therapy with low-dose methotrexate regressed completely following withdrawal of methotrexate. If lymphoproliferative disease occurs, discontinue Methotrexate Injection and institute appropriate treatment if lymphoma does not regress.

5.14 Tumor Lysis Syndrome

Methotrexate can induce tumor lysis syndrome in patients with rapidly growing tumors. Institute appropriate treatment for prevention and management of tumor lysis syndrome.

5.15 Immunization and Risks Associated with Live Vaccines

Immunization during Methotrexate Injection treatment may be ineffective.

Disseminated infections following administration of live vaccines have been reported.

Update immunizations according to immunization guidelines prior to initiating Methotrexate Injection. Immunization with live vaccines is not recommended during treatment. The interval between live vaccinations and initiation of Methotrexate Injection should be in accordance with current vaccination guidelines for patients on immunosuppressive therapies.

5.16 Infertility

Based on published reports, methotrexate can cause impairment of fertility, oligospermia, and menstrual dysfunction. It is not known if the infertility may be reversible in affected patients. Discuss the risk of effects on reproduction with female and male patients of reproductive potential [see Use in Specific Populations (8.3)].

5.17 Increased Risk of Adverse Reactions Due to Third-Space Accumulation

Methotrexate can exit slowly from third-space accumulations resulting in prolonged terminal plasma half-life and toxicity. Evacuate significant third-space accumulations prior to Methotrexate Injection administration [see Clinical Pharmacology (12.3)].

5.18 Increased Risk of Soft Tissue and Bone Toxicity with Concomitant Radiotherapy

Concomitant radiation therapy increases the risk of soft tissue necrosis and osteonecrosis associated with methotrexate.

5.19 Risk of Serious Adverse Reactions with Medication Errors

Serious adverse reactions, including death, have occurred due to medication errors. Most commonly, these errors occurred in patients who were taking methotrexate daily when a weekly dosing regimen was prescribed. Ensure that patients receive the recommended dosage, because medication errors have led to death.

6 ADVERSE REACTIONS

The following adverse reactions are described, or described in greater detail, in other sections:

- Hypersensitivity Reactions [see Warnings and Precautions (5.2)]
- Myelosuppression [see Warnings and Precautions (5.4)]
- Serious Infections [see Warnings and Precautions (5.5)]
- Renal Toxicity [see Warnings and Precautions (5.6)]
- Hepatotoxicity [see Warnings and Precautions (5.7)]
- Neurotoxicity [see Warnings and Precautions (5.8)]
- Gastrointestinal Toxicity [see Warnings and Precautions (5.9)]
- Pulmonary Toxicity [see Warnings and Precautions (5.10)]
- Dermatologic Reactions [see Warnings and Precautions (5.11)]
- Secondary Malignancies [see Warnings and Precautions (5.13)]
- Tumor Lysis Syndrome [see Warnings and Precautions (5.14)]
- Increased Risk of Adverse Reactions due to Third-Space Accumulation [see Warnings and Precautions (5.17)]

6.1 Clinical Trials Experience

Because clinical trials and other studies are conducted under widely varying conditions, adverse reaction rates observed in the clinical trials of a drug cannot be directly compared to rates in the clinical trials of another drug and may not reflect the rates observed in practice.

Commonly reported adverse reactions include ulcerative stomatitis, leukopenia, nausea, and abdominal distress. Other frequently reported adverse reactions are infection, malaise, fatigue, chills, fever, and dizziness.

Rheumatoid Arthritis

The approximate incidences of methotrexate-attributed (i.e., placebo rate subtracted) adverse reactions in 12- to 18-week double-blind studies in patients (n = 128) with RA treated with low-dose oral (7.5 mg per week to 15 mg per week) pulse methotrexate are listed below. Most patients were on concomitant NSAIDs and some received corticosteroids. Hepatic histology was not examined in these short-term studies.

Incidence ≥10%: Elevated liver function tests 15%, nausea/vomiting 10%.

Incidence 3% to <10%: Stomatitis, thrombocytopenia (platelet count less than 100,000/mm^3).

Incidence 1% to <3%: Rash/pruritus/dermatitis, diarrhea, alopecia, leukopenia (white blood cell count less than 3000/mm^3), pancytopenia, dizziness.

Two other controlled trials of patients (n = 680) with RA on 7.5 mg per week to 15 mg per week oral doses showed the following adverse reactions:

Incidence 1%: Interstitial pneumonitis.

Other less common adverse reactions: Decreased hematocrit, headache, upper respiratory infection, anorexia, arthralgias, chest pain, coughing, dysuria, eye discomfort, epistaxis, fever, infection, sweating, tinnitus, vaginal discharge.

Polyarticular Juvenile Idiopathic Arthritis (pJIA)

The approximate incidences of adverse reactions reported in patients 2 to 18 years of age with pJIA treated with oral, weekly doses of methotrexate (5 mg/m^2 per week to 20 mg/m^2 per week or 0.1 mg/kg per week to 0.65 mg/kg per week) were as follows (most patients were receiving concomitant NSAIDs, and some received corticosteroids): elevated liver function tests, 14%; gastrointestinal reactions (e.g., nausea, vomiting, diarrhea), 11%; stomatitis, 2%; leukopenia, 2%; headache, 1.2%; alopecia, 0.5%; dizziness, 0.2%; rash, 0.2%.

Psoriasis

In two published series of adult psoriasis patients (n = 204, 248) treated with methotrexate doses up to 25 mg per week for up to 4 years, adverse reaction rates were similar to those in patients with RA, except for alopecia, photosensitivity, and "burning of skin lesions" (each 3% to 10%). Painful plaque erosions have been reported.

6.2 Postmarketing Experience

The following adverse reactions have been identified during post-approval use of methotrexate. Because these reactions are reported voluntarily from a population of uncertain size, it is not always possible to reliably estimate their frequency or establish a causal relationship to drug exposure.

Blood and lymphatic system disorders: Aplastic anemia, lymphadenopathy, hypogammaglobulinemia

Cardiovascular disorders: Thromboembolic events (including arterial thrombosis, cerebral thrombosis, deep vein thrombosis, retinal vein thrombosis, thrombophlebitis, and pulmonary embolus), pericarditis, pericardial effusion, hypotension, sudden death

Endocrine: Diabetes

Eye disorders: Optic neuropathy, blurred vision, ocular irritation, conjunctivitis, xerophthalmia

Gastrointestinal disorders: Hemorrhagic enteritis, intestinal perforation, gingivitis, pancreatitis, pharyngitis, hematemesis, melena, gastrointestinal ulceration and bleeding

Hepatobiliary disorders: Acute hepatitis, decreased serum albumin, fibrosis, cirrhosis, liver failure

Immune system disorders: Anaphylaxis, anaphylactoid reactions, vasculitis

Metabolism: Hyperglycemia

Musculoskeletal disorders: Stress fracture, soft tissue necrosis, arthralgia, myalgia, osteoporosis

Nervous system disorders: Headaches, drowsiness, blurred vision, speech impairment (including dysarthria and aphasia), transient cognitive dysfunction, mood alteration, unusual cranial sensations, paresis, encephalopathy, leukoencephalopathy, and convulsions. Also, spinal radiculopathy with intrathecal use

Renal disorders: Severe renal toxicity including renal failure, azotemia, hematuria, proteinuria, cystitis

Reproductive disorders: Defective oogenesis or spermatogenesis, loss of libido, impotence, gynecomastia, menstrual dysfunction

Respiratory disorders: Pulmonary fibrosis, respiratory failure, chronic interstitial obstructive pulmonary disease, pleuritic pain and thickening, alveolitis

Skin disorders: Toxic epidermal necrolysis, Stevens-Johnson syndrome, exfoliative dermatitis, skin necrosis, and erythema multiforme, erythematous rashes, pruritus, alopecia, skin ulceration, accelerated nodulosis, urticaria, pigmentary changes, ecchymosis, telangiectasia, photosensitivity, acne, furunculosis

General disorders and administration site conditions: Injection site necrosis, injection site reaction

7 DRUG INTERACTIONS

7.1 Effects of Other Drugs on Methotrexate

Drugs that Increase Methotrexate Exposure

Coadministration of methotrexate with the following products may increase methotrexate plasma concentrations, which may increase the risk of methotrexate severe adverse reactions.

Increased organ specific adverse reactions may also occur when methotrexate is coadministered with hepatotoxic or nephrotoxic products. If coadministration cannot be avoided, monitor closely for methotrexate adverse reactions when coadministered with:

- Penicillin or sulfonamide antibiotics
- Highly protein bound drugs (e.g., oral anticoagulants, phenytoin, salicylates, sulfonamides, sulfonylureas, and tetracyclines)
- Proton pump inhibitors
- Probenecid
- Antifolate drugs (e.g., dapsone, pemetrexed, pyrimethamine and sulfonamides)
- Aspirin and other nonsteroidal anti-inflammatory drugs
  Unexpectedly severe and fatal gastrointestinal toxicity can occur with concomitant administration of methotrexate (primarily at high-dose) and nonsteroidal anti-inflammatory drugs (NSAIDs).
- Mercaptopurine
- Hepatotoxic products
- Weak acids (e.g., salicylates)
- Nephrotoxic products
- Hematotoxic agents

Nitrous Oxide

Coadministration of methotrexate with nitrous oxide anesthesia potentiates the effect of methotrexate on folate-dependent metabolic pathways, which may increase the risk of severe methotrexate adverse reactions. Avoid nitrous oxide anesthesia in patients receiving methotrexate. Consider alternative therapies in patients who have received prior nitrous oxide anesthesia.

Folic Acid

Coadministration of methotrexate with folic acid or its derivatives decreases the clinical effectiveness of methotrexate in patients with neoplastic diseases. Methotrexate competes with reduced folates for active transport across cell membranes. Instruct patients to take folic or folinic acid only as directed by their healthcare provider [see Warnings and Precautions (5.12)].

7.2 Effects of Methotrexate on Other Drugs

Theophylline

Coadministration of methotrexate with theophylline increases theophylline plasma concentrations which may increase the risk of theophylline adverse reactions. Monitor theophylline levels and adjust the theophylline dosage in accordance with approved product labeling.

8 USE IN SPECIFIC POPULATIONS

8.1 Pregnancy

Risk Summary

Methotrexate Injection is contraindicated in pregnant women with non-neoplastic diseases. Based on published reports and its mechanism of action, methotrexate can cause embryo-fetal toxicity and fetal death when administered to a pregnant woman [see Data and Clinical Pharmacology (12.1)]. There are no animal data that meet current standards for nonclinical developmental toxicity studies. Advise pregnant women with neoplastic diseases of the potential risk to a fetus. The preservative benzyl alcohol can cross the placenta; when possible, use the preservative-free formulation when Methotrexate Injection is needed during pregnancy to treat a neoplastic disease [see Warnings and Precautions (5.3) and Use in Specific Populations (8.4)].

In the U.S. general population, the estimated background risk of major birth defects and miscarriage in clinically recognized pregnancies is 2–4% and 15–20%, respectively.

Data

Human Data

Published data from case reports, literature reviews, and observational studies report that methotrexate exposure during pregnancy is associated with an increased risk of embryo-fetal toxicity and fetal death. Methotrexate exposure during the first trimester of pregnancy is associated with an increased incidence of spontaneous abortions and multiple adverse developmental outcomes, including skull anomalies, facial dysmorphism, CNS abnormalities, limb abnormalities, and sometimes cardiac anomalies and intellectual impairment. Adverse outcomes associated with exposure during second and third trimesters of pregnancy include intrauterine growth restriction and functional abnormalities. Because methotrexate is widely distributed and persists in the body for a prolonged period, there is a potential risk to the fetus from preconception methotrexate exposure.

A prospective multicenter study evaluated pregnancy outcomes in women taking methotrexate less than or equal to 30 mg per week after conception. The rate of spontaneous abortion/miscarriage in pregnant women exposed to methotrexate was 42.5% (95% confidence interval [95% CI] 29.2–58.7), which was higher than in unexposed patients with autoimmune disease (22.5%, 95% CI 16.8–29.7) and unexposed patients with non-autoimmune disease (17.3%, 95% CI 13–22.8). Of the live births, the rate of major birth defects in pregnant women exposed to methotrexate after conception was higher than in unexposed patients with autoimmune disease (adjusted odds ratio (OR) 1.8 [95% CI 0.6–5.7]) and unexposed patients with non-autoimmune disease (adjusted OR 3.1 [95% CI 1.03–9.5]) (2.9%). Major birth defects associated with pregnancies exposed to methotrexate after conception were not always consistent with methotrexate-associated adverse developmental outcomes.

8.2 Lactation

Risk Summary

Limited published literature reports the presence of methotrexate in human milk in low amounts, with the highest breast milk to plasma concentration ration reported to be 0.08:1. No information is available on the effects of methotrexate on a breastfed infant or on milk production. Because of the potential for serious adverse reactions from methotrexate in breastfed infants, advise women not to breastfeed during treatment with Methotrexate Injection and for 1 week after the last dose.

8.3 Females and Males of Reproductive Potential

Methotrexate can cause malformations and fetal death at doses less than or equal to the recommended clinical doses [see Use in Specific Populations (8.1)].

Pregnancy Testing

Verify the pregnancy status of females of reproductive potential prior to initiating Methotrexate Injection [see Contraindications (4) and Use in Specific Populations (8.1)].

Contraception

Females

Advise females of reproductive potential to use effective contraception during and for 6 months after the last dose of Methotrexate Injection therapy.

Males

Methotrexate can cause chromosomal damage to sperm cells. Advise males with female partners of reproductive potential to use effective contraception during and for 3 months after the last dose of Methotrexate Injection therapy.

Infertility

Females

Based on published reports of female infertility after therapy with methotrexate, advise females of reproductive potential that Methotrexate Injection can cause impairment of fertility and menstrual dysfunction during and after cessation of therapy. It is not known if the infertility may be reversed in all affected females.

Males

Based on published reports of male infertility after therapy with methotrexate, advise males that Methotrexate Injection can cause oligospermia or infertility during and after cessation of therapy. It is not known if the infertility may be reversed in all affected males.

8.4 Pediatric Use

The safety and effectiveness of Methotrexate Injection in pediatric patients have been established for ALL, meningeal leukemia prophylaxis and treatment, non-Hodgkin lymphoma, osteosarcoma and in pJIA. Clinical studies evaluating the use of methotrexate in pediatric patients with pJIA demonstrated safety comparable to that observed in adults with RA [see Adverse Reactions (6.1)]. The safety and effectiveness of Methotrexate Injection have not been established in pediatric patients for the treatment of breast cancer, squamous cell carcinoma of the head and neck, gestational trophoblastic neoplasia, rheumatoid arthritis, and psoriasis. Additional risk information is described below.

Risks of Serious Adverse Reactions due to Benzyl Alcohol-Preservative

Due to the risk of serious adverse reactions and fatal gasping syndrome following administration of intravenous solutions containing the preservative benzyl alcohol in neonates, use only preservative-free Methotrexate Injection in neonates and low birth weight infants. The "gasping syndrome" is characterized by CNS depression, metabolic acidosis, and gasping respirations.

Serious adverse reactions including fatal reactions and the "gasping syndrome" occurred in premature neonates and low birth weight infants in the neonatal intensive care unit who received drugs containing benzyl alcohol as a preservative. In these cases, benzyl alcohol dosages of 99 to 234 mg/kg/day produced high levels of benzyl alcohol and its metabolites in the blood and urine (blood levels of benzyl alcohol were 0.61 to 1.378 mmol/L). Additional adverse reactions include gradual neurological deterioration, seizures, intracranial hemorrhage, hematological abnormalities, skin breakdown, hepatic and renal failure, hypotension, bradycardia, and cardiovascular collapse. Preterm, low birth weight infants may be more likely to develop these reactions because they may be less able to metabolize benzyl alcohol.

When prescribing in infants (non-neonate, non-low birth weight), if a preservative-free formulation of Methotrexate Injection is not available and use of a benzyl alcohol-containing formulation is necessary, consider the combined daily metabolic load of benzyl alcohol from all sources including Methotrexate Injection (Methotrexate Injection contains 9.4 mg of benzyl alcohol per mL) and other drugs containing benzyl alcohol. The minimum amount of benzyl alcohol at which serious adverse reactions may occur is not known.

Do not administer methotrexate formulations containing benzyl alcohol intrathecally due to the risk of severe neurotoxicity [see Warnings and Precautions (5.3)].

Leukemia/Lymphoma

Serious neurotoxicity, frequently manifested as generalized or focal seizures, has been reported with unexpectedly increased frequency among pediatric patients with acute lymphoblastic leukemia who were treated with intermediate-dose intravenous methotrexate (1 g/m^2) [see Warnings and Precautions (5.8)].

8.5 Geriatric Use

Clinical studies of methotrexate did not include sufficient numbers of subjects aged 65 and over to determine whether they respond differently from younger subjects.

8.6 Renal Impairment

Methotrexate elimination is reduced in patients with renal impairment [creatinine clearance (CLcr) less than 90 mL/min, calculated using Cockcroft-Gault] [see Clinical Pharmacology (12.3)]. Patients with renal impairment are at increased risk for methotrexate adverse reactions.

Follow recommendations to promote methotrexate elimination and decrease risk of acute kidney injury and other methotrexate toxicities in patients who are receiving intermediate- or high-dose regimens [see Dosage and Administration (2.2) and Warnings and Precautions (5.6)]. Consider reducing the dose or discontinuing Methotrexate Injection in patients with renal impairment as appropriate.

8.7 Hepatic Impairment

The pharmacokinetics and safety of methotrexate in patients with hepatic impairment is unknown. Patients with hepatic impairment may be at increased risk for methotrexate adverse reaction based on elimination characteristics of methotrexate [see Clinical Pharmacology (12.3)]. Consider reducing the dose or discontinuing Methotrexate Injection in patients with hepatic impairment as appropriate [see Warnings and Precautions (5.7)].

10 OVERDOSAGE

Manifestations

Overdosage, including fatal overdosage, has occurred with methotrexate [see Warnings and Precautions (5.19)].

Manifestations of overdosage include adverse reactions reported at pharmacologic doses, particularly hematologic and gastrointestinal reactions (e.g., leukopenia, thrombocytopenia, anemia, pancytopenia, myelosuppression, mucositis, stomatitis, oral ulceration, nausea, vomiting, gastrointestinal ulceration, or gastrointestinal bleeding). In some cases, no symptoms were reported; however, sepsis or septic shock, renal failure, and aplastic anemia were also reported.

Manifestations of intrathecal overdosage include CNS symptoms (e.g., headache, nausea and vomiting, seizure or convulsion, and acute toxic encephalopathy). In some cases, no symptoms were reported; however, cerebellar herniation associated with increased intracranial pressure and acute toxic encephalopathy have also been reported.

Management

Leucovorin and levoleucovorin are indicated to diminish the toxicity and counteract the effect of inadvertently administered overdosages of methotrexate. Administer leucovorin or levoleucovorin as soon as possible after overdosage (refer to the leucovorin or levoleucovorin prescribing information). Monitor serum methotrexate concentrations closely to guide leucovorin or levoleucovorin therapy. Monitor serum creatinine concentrations closely because high serum methotrexate concentrations may cause renal damage leading to acute renal failure.

Glucarpidase is indicated for the treatment of toxic methotrexate concentrations in patients with delayed methotrexate clearance due to impaired renal function (refer to the glucarpidase prescribing information). If glucarpidase is used, do not administer leucovorin within 2 hours before or after a dose of glucarpidase because leucovorin is a substrate for glucarpidase.

Hydration and urinary alkalinization may be necessary to prevent the precipitation of methotrexate and/or its metabolites in the renal tubules. Neither hemodialysis nor peritoneal dialysis has been shown to improve methotrexate elimination. However, effective clearance of methotrexate has been reported with acute, intermittent hemodialysis using a high-flux dialyzer.

11 DESCRIPTION

Methotrexate is a folate analog metabolic inhibitor with the chemical name of N-[4-[[(2,4-diamino-6-pteridinyl) methyl]methylamino]benzoyl]-L-glutamic acid and a molecular weight of 454.44. The molecular formula is C20H22N8O5 , and the structural formula is shown below:

Methotrexate Injection with preservative is supplied in sterile multiple-dose vials for intravenous, intramuscular, or subcutaneous use.

- Each 25 mg/mL, 2 mL vial contains 50 mg methotrexate equivalent to 54.8 mg of methotrexate sodium, 18.8 mg of benzyl alcohol as a preservative and Sodium chloride 5.2 mg. May contain sodium hydroxide and/or hydrochloric acid to adjust the pH to 8.5.

Preservative-free Methotrexate Injection is supplied in sterile single-dose vials for intravenous, intramuscular, subcutaneous, or intrathecal use.

- Each 25 mg/mL, 40 mL vial contains 1000 mg methotrexate equivalent to 1096.7 mg of methotrexate sodium, and the following inactive ingredients: Sodium chloride 196 mg. May contain sodium hydroxide and/or hydrochloric acid to adjust pH to 8.5.

12 CLINICAL PHARMACOLOGY

12.1 Mechanism of Action

Methotrexate inhibits dihydrofolic acid reductase. Dihydrofolates must be reduced to tetrahydrofolates by this enzyme before they can be utilized as carriers of one-carbon groups in the synthesis of purine nucleotides and thymidylate. Therefore, methotrexate interferes with DNA synthesis, repair, and cellular replication. Actively proliferating tissues such as malignant cells, bone marrow, fetal cells, buccal and intestinal mucosa, and cells of the urinary bladder are in general more sensitive to this effect of methotrexate.

The mechanism of action in rheumatoid arthritis, pJIA, and in psoriasis is unknown.

12.3 Pharmacokinetics

Distribution

After intravenous administration, the initial volume of distribution is approximately 0.18 L/kg (18% of body weight) and steady-state volume of distribution is approximately 0.4 L/to 0.8 L/kg (40% to 80% of body weight).

Methotrexate competes with reduced folates for active transport across cell membranes by means of a single carrier-mediated active transport process. At serum concentrations greater than 100 micromolar, passive diffusion becomes a major pathway by which effective intracellular concentrations can be achieved.

Methotrexate in serum is approximately 50% protein bound.

Methotrexate may be displaced from plasma albumin by various compounds, including sulfonamides, salicylates, tetracyclines, chloramphenicol, and phenytoin.

Methotrexate does not penetrate the blood-cerebrospinal fluid barrier in therapeutic amounts when given intravenously, intramuscularly, or subcutaneously.

Elimination

The terminal half-life reported for methotrexate is approximately 3 to 10 hours for patients receiving treatment for psoriasis, or rheumatoid arthritis or low-dose antineoplastic therapy (less than 30 mg/m^2).

Following intravenous administration of high-dose methotrexate, the terminal half-life is 8 hours to 15 hours.

Metabolism

Methotrexate undergoes hepatic and intracellular metabolism to polyglutamated forms that can be converted back to methotrexate by hydrolase enzymes. These polyglutamates act as inhibitors of dihydrofolate reductase and thymidylate synthetase. Small amounts of methotrexate polyglutamates may remain in tissues for extended periods. The retention and prolonged drug action of these active metabolites vary among different cells, tissues, and tumors. Methotrexate undergoes minor metabolism to 7-hydroxymethotrexate, and accumulation may become significant following high dosages. The aqueous solubility of 7-hydroxymethotrexate is 3- to 5-fold lower than the solubility of methotrexate.

Excretion

Renal excretion is the primary route of elimination and is dependent upon dosage and route of administration. With intravenous administration, 80% to 90% of the administered dose is excreted unchanged in the urine within 24 hours. There is limited biliary excretion amounting to 10% or less of the administered dose. Enterohepatic recirculation of methotrexate has been proposed.

Renal excretion occurs by glomerular filtration and active tubular secretion. Nonlinear elimination due to saturation of renal tubular reabsorption has been observed in psoriatic patients at doses between 7.5 mg and 30 mg.

Specific Populations

Pediatric Patients

In pediatric patients receiving methotrexate for acute lymphoblastic leukemia (6.3 mg/m^2 to 30 mg/m^2), or for JIA (3.75 mg/m^2 to 26.2 mg/m^2), the terminal half-life has been reported to range from 0.7 to 5.8 hours or from 0.9 to 2.3 hours, respectively [see Use in Specific Populations (8.4)].

Patients with Renal impairment

The elimination half-life of methotrexate increases with the severity of renal impairment, with high inter-individual variability [see Use in Specific Populations (8.6)].

13 NONCLINICAL TOXICOLOGY

13.1 Carcinogenesis, Mutagenesis, Impairment of Fertility

Methotrexate has been evaluated in a number of animal studies for carcinogenic potential with inconclusive results. There is evidence that methotrexate causes chromosomal damage to animal somatic cells and human bone marrow cells [see Use in Specific Populations (8.1, 8.2, 8.3)].

15 REFERENCES

1. "OSHA Hazardous Drugs." OSHA. http://www.osha.gov/SLTC/hazardousdrugs/index.html.

16 HOW SUPPLIED/STORAGE AND HANDLING

How Supplied

Methotrexate Injection is a clear, yellow, sterile solution available with preservative (multiple-dose vials) and preservative-free (single-dose vials) as follows:

Strength/Fill volume | NDC number | Pack style
With Preservative
50 mg/2 mL (25 mg/mL) | 61703-350-10 | Carton containing five (5) multiple-dose vials
Preservative-free
1 g/40 mL (25 mg/mL) | 61703-408-25 | Carton containing one (1) single-dose vial

Carton contents | NDC
Methotrexate Injection, With Preservative, 5 multiple-dose vials
50 mg/2 mL (25 mg/mL) | 61703-350-10
Preservative-free Methotrexate Injection, 1 single-dose vial
1 g/40 mL (25 mg/mL) | 61703-408-25

Storage and Handling

Store at 20°C to 25°C (68°F to 77°F); excursions permitted to 15°C to 30°C (59°F to 86°F) [see USP Controlled Room Temperature]. Protect from light.

After first puncture, store multiple-dose vials at 2°C to 8°C, and use within 30 days.

Methotrexate Injection is a hazardous drug. Follow applicable special handling and disposal procedures.^1

17 PATIENT COUNSELING INFORMATION

Advise the patient to read the FDA-approved patient labeling (Patient Information).

Embryo-Fetal Toxicity

- Advise females of reproductive potential of the potential risk to a fetus and to inform their healthcare provider of a known or suspected pregnancy [see Contraindications (4), Warnings and Precautions (5.1), and Use in Specific Populations (8.1)].
- Advise females of reproductive potential to use effective contraception during Methotrexate Injection therapy and for 6 months after the last dose [see Use in Specific Populations (8.3)].
- Advise males of reproductive potential to use effective contraception during Methotrexate Injection therapy and for 3 months after the last dose [see Use in Specific Populations (8.3)].

Hypersensitivity Reactions

Advise patients of the potential risk of hypersensitivity and that Methotrexate Injection is contraindicated in patients with a history of severe hypersensitivity to methotrexate. Advise patients to seek immediate medical attention if signs or symptoms of a hypersensitivity reaction occur [see Warnings and Precautions (5.2)].

Myelosuppression and Serious Infections

Advise patient to contact their healthcare provider immediately for new onset fever, symptoms of infection, easy bruising or persistent bleeding [see Warnings and Precautions (5.4, 5.5)].

Renal Toxicity

Advise patients that methotrexate can cause renal toxicity. Advise patients to immediately contact their healthcare provider for signs or symptoms of renal toxicity, such as marked increases or decreases in urinary output [see Warnings and Precautions (5.6)].

Hepatotoxicity

Advise patients to report signs or symptoms of hepatic toxicity and avoidance of alcohol during methotrexate treatment [see Warnings and Precautions (5.7)].

Neurotoxicity

Advise patient to contact their healthcare provider immediately if they develop new neurological symptoms [see Warnings and Precautions (5.8)].

Gastrointestinal Toxicity

Advise patients to contact their healthcare provider if they develop diarrhea, vomiting, or stomatitis. Advise patients to immediately contact their healthcare provider for high fever, rigors, persistent or severe abdominal pain, severe constipation, hematemesis, or melena [see Warnings and Precautions (5.9)].

Pulmonary Toxicity

Advise patients to contact their healthcare provider for symptoms of cough, fever, and dyspnea [see Warnings and Precautions (5.10)].

Dermatologic Toxicity

Advise patients that Methotrexate Injection can cause serious skin rash and to immediately contact their healthcare provider for new or worsening skin rash. Advise patients to avoid excessive sun exposure and to use sun protection measures [see Warnings and Precautions (5.11)].

Secondary Malignancies

Advise patients on the risk of second primary malignancies during treatment with Methotrexate Injection [see Warnings and Precautions (5.13)].

Lactation

Advise women not to breastfeed during treatment with Methotrexate Injection and for 1 week after the last dose [see Use in Specific Populations (8.2)].

Infertility

Advise females and males of reproductive potential that Methotrexate Injection may cause impairment of fertility [see Use in Specific Populations (8.3)].

Drug Interactions

- Advise patients and caregivers to inform their healthcare provider of all concomitant medications, including prescription medicines, over-the-counter drugs, vitamins, and herbal products [see Drug Interactions (7)].
- Instruct patients being treated for neoplastic indication to not take products containing folic acid or folinic acid unless directed to do so by their healthcare provider [see Warnings and Precautions (5.12)].

Distributed by Hospira, Inc., Lake Forest, IL 60045

Novaplus is a registered trademark of Vizient, Inc.

LAB-1000-6.0

Patient Information
METHOTREXATE (Meth-oh-trex-ate)
Injection
for intravenous, intramuscular,
subcutaneous, or intrathecal use

What is the most important information I should know about Methotrexate Injection?

Methotrexate Injection can cause serious side effects that may be severe and lead to death, including:

Harm to an unborn baby, including birth defects or death of an unborn baby.

Females who can become pregnant:

- Your healthcare provider should do a pregnancy test before you start taking Methotrexate Injection to see if you are pregnant.
- If you are being treated for a medical condition other than cancer, do not receive or take Methotrexate Injection if you are pregnant. See “Do not receive Methotrexate Injection if”.
- If you are taking Methotrexate Injection to treat your cancer, you and your healthcare provider will decide if you will receive or take Methotrexate Injection if you are pregnant.
- Use effective birth control (contraception) during treatment and for 6 months after your last dose of Methotrexate Injection. Ask your healthcare provider what forms of birth control you can use during this time.
  Tell your healthcare provider right away if you become pregnant or think you are pregnant during treatment with Methotrexate Injection.

Males with female partners who are able to become pregnant:

- Use effective birth control during treatment and for 3 months after your last dose of Methotrexate Injection.
  Tell your healthcare provider right away if your female partner becomes pregnant during treatment with Methotrexate Injection.

Severe allergic reactions. Severe allergic reactions can happen with Methotrexate Injection.

- Do not receive Methotrexate Injection if you have had a severe allergic reaction to methotrexate in the past.
  Get medical help right away if you develop any of the signs or symptoms of a severe allergic reaction to Methotrexate Injection, including:

- skin rash, itching, and hives
- swelling of the face, lips, tongue, or throat, or trouble swallowing
- dizziness or lightheadedness
- trouble breathing
- wheezing

- throat tightness
- runny or stuffy nose
- fast heart rate
- chest pain
- feeling faint

Decreased blood cell counts. Methotrexate Injection can affect your bone marrow and cause decreased red blood cell counts, white blood cell counts, and platelet counts, and a condition where your bone marrow cannot produce these blood cells (aplastic anemia). These decreased blood cell counts can be severe and may lead to a serious infection, the need for blood transfusions, treatment in a hospital, and can be life-threatening. Your healthcare provider will check your blood cell counts before you start and during treatment with Methotrexate Injection. Your healthcare provider will watch you closely for infections during treatment with Methotrexate Injection.

Call your healthcare provider right away if you develop:

- a new fever (temperature of 100.4°F or higher)

- symptoms of infection

- easy bruising or bleeding that will not stop

Your healthcare provider may give you medicines to support your blood counts or give you transfusions if needed, and change your dose or stop your treatment with Methotrexate Injection if needed.

Serious infections. People who receive treatment with Methotrexate Injection have an increased risk of developing serious infections that can be life-threatening or lead to death. These infections include:

- bacterial infections
- fungal infections
- viral infections
- certain infections that happen because your immune system is weakened

- hepatitis B infection that comes back (reactivation)
- tuberculosis (TB) infection that is new or that comes back (reactivation)
- shingles (herpes zoster)
- cytomegalovirus infections

Your healthcare provider will closely watch you for signs and symptoms of infection during treatment with Methotrexate Injection. Your healthcare provider may hold or stop your treatment with Methotrexate Injection if you develop a serious infection.

Kidney problems. Methotrexate Injection can cause kidney damage including sudden kidney failure that may not go away (irreversible). People who already have kidney problems have an increased risk of kidney problems with Methotrexate Injection. Your healthcare provider will check your kidney function during treatment, and will hold or stop Methotrexate Injection treatment as needed for severe kidney damage.

Call your healthcare provider right away if you have signs or symptoms of kidney problems such as a big change in the amount of urine that you make, either increased or decreased.

Liver problems. Methotrexate Injection can cause severe liver problems including liver scarring (fibrosis), cirrhosis, and liver failure that may not get better (possibly irreversible) and can cause death.

- In people with psoriasis who receive Methotrexate Injection, liver fibrosis or cirrhosis may happen without any symptoms or abnormal liver tests. The risk for liver problems in people with psoriasis increases with the amount of Methotrexate Injection that you receive over time.
- Your healthcare provider will do tests to monitor your liver function before you start and during treatment with Methotrexate Injection, and may hold or stop your treatment with Methotrexate Injection, if needed.
- The risk of liver problems is increased with heavy use of alcohol. Avoid drinking alcohol during Methotrexate Injection treatment.

Tell your healthcare provider if you develop any signs or symptoms of liver problems during treatment with Methotrexate Injection, including:

- tiredness
- easy bleeding or bruising
- loss of appetite
- nausea
- difficulty thinking clearly

- swelling in your legs, feet, or ankles
- weight loss
- itchy skin
- yellowing of your skin or the white part of your eyes
- weakness

Brain and spinal cord (nervous system) problems. Methotrexate Injection can cause nervous system problems that can be severe and last for a short time or last for a long time. These nervous system problems can get progressively worse, may not get better (possibly irreversible), and can cause death.

- Serious nervous system problems can happen in children who receive Methotrexate Injection, including seizures that can begin on one side of the brain (focal seizures) or on both sides of the brain (generalized seizures).
- The risk for a nervous system problem called leukoencephalopathy is increased in people who have had radiation treatment to their head and spine (craniospinal irradiation) in the past. Call your healthcare provider if you develop any new neurological symptoms.
- People who receive high-dose Methotrexate Injection can develop sudden symptoms that are like the symptoms of a stroke, but they last a short time and may go away (transient).
- People who receive injections of Methotrexate Injection into their spine (intrathecal methotrexate) can develop inflammation of the lining around the spinal nerves.

Call your healthcare provider right away if you or your child develop any new signs or symptoms of a nervous system problem during treatment with Methotrexate Injection, including:

- confusion
- weakness on one side of your body
- sudden blindness that goes away
- seizures

- coma
- headache
- back pain
- stiff neck
- fever

Severe stomach and intestine (gastrointestinal) problems.
Methotrexate Injection can cause diarrhea, vomiting, mouth sores, stomach and intestinal inflammation with severe bleeding, and tears in the intestinal wall (perforation), and can lead to death.

- People who have stomach ulcers (peptic ulcer disease) or ulcerative colitis (UC) have a higher risk of developing severe stomach and intestine problems with Methotrexate Injection.
- Your healthcare provider may hold or stop your treatment with Methotrexate Injection if any of these severe stomach and intestinal problems happen, and treat you as needed.
- Call your healthcare provider if you develop diarrhea, vomiting, inflammation or sores in your mouth.

Call your healthcare provider right away if you develop:

- high fever
- shaking chills
- stomach-area (abdomen) pain that is severe or does not go away.

- severe constipation
- if you are vomiting blood
- blood in your stools

Lung problems. Lung problems can happen suddenly (acute) with Methotrexate Injection or they can develop over a long period-of-time (chronic). Lung problems may not get better (possibly irreversible) and can cause death in anyone taking Methotrexate Injection. Your healthcare provider will monitor you for lung problems during treatment with Methotrexate Injection. Your healthcare provider may hold or stop your treatment with Methotrexate Injection, if needed.

Call your healthcare provider if you develop symptoms of a lung problem, including: cough, fever, and trouble breathing.

Skin reactions. Severe skin reactions can happen with Methotrexate Injection, that can be serious and can lead to death.

- In people with psoriasis: Your psoriasis may get worse if you are exposed to sunlight or other types of ultraviolet light.
- Methotrexate Injection can cause reactivation of skin reactions that can happen after radiation therapy (radiation recall), sunburns to come back (photodermatitis) and severe sunburn reactions.

Limit sunlight exposure during treatment with Methotrexate Injection. Use a broad-spectrum ultraviolet sunscreen and lip balm with a Sun Protection Factor (SPF) of 30 or greater and wear a hat and protective clothing when you will be exposed to sunlight during treatment with Methotrexate Injection.

Call your healthcare provider right away if you develop a new or worsening skin rash during treatment with Methotrexate Injection.

See “What are the possible side effects of Methotrexate Injection?” for more information about side effects.

What is Methotrexate Injection?
Methotrexate Injection is a prescription medicine used:
in adults and children:

- in combination with other chemotherapy medicines to treat acute lymphoblastic leukemia (ALL) to help prevent (prophylaxis) and to treat leukemia that spreads to the covering of the brain and spinal cord (meninges)
- to treat non-Hodgkin lymphoma
- in combination with other chemotherapy medicines to treat osteosarcoma

in adults:

- in combination with other chemotherapy medicines to treat breast cancer
- alone to treat squamous cell carcinoma of the head and neck
- in combination with other chemotherapy medicines to treat gestational trophoblastic neoplasia

Methotrexate Injection is a prescription medicine used:

- in adults to treat rheumatoid arthritis (RA)
- in children to treat polyarticular juvenile idiopathic arthritis (pJIA)
- in adults to treat severe psoriasis

Do not receive Methotrexate Injection if you:

- have had a severe allergic reaction to Methotrexate Injection. See “What is the most important information I should know about Methotrexate Injection?”
- you are pregnant and are being treated, or will be treated with Methotrexate Injection for rheumatoid arthritis, pJIA, or severe psoriasis, or for any disease other than cancer. Methotrexate Injection can cause harm to an unborn baby including birth defects or death of an unborn baby. See “What is the most important information I should know about Methotrexate Injection?”

Before you receive Methotrexate Injection, tell your healthcare provider about all of your medical conditions, including if you:

- have kidney problems or are receiving dialysis treatments
- have liver problems
- have a history of neurologic problems, including seizures
- drink alcohol-containing beverages during treatment with Methotrexate Injection, or if there are any changes in the amount of alcoholic beverages you drink
- have fluid in your stomach-area (ascites)
- have lung problems or fluid in your lungs (pleural effusion)
- plan to have any surgeries with general anesthesia, including dental surgery
- have stomach ulcers (peptic ulcer disease)
- have ulcerative colitis
- have recently received or are scheduled to receive a vaccine. You should not receive live vaccines during treatment with Methotrexate Injection.
- are breastfeeding or plan to breastfeed. Methotrexate may pass into your breast milk. Do not breastfeed during treatment and for 1 week after your last dose of Methotrexate Injection.

Tell your healthcare provider about all the medicines you take, including prescription and over-the-counter medicines, vitamins, and herbal supplements. Taking certain medicines can affect the amount of methotrexate in your blood and can increase your risk for serious side effects.

How will I receive or take Methotrexate Injection?

- Depending on your medical condition and the dose of Methotrexate Injection that is prescribed by your healthcare provider, Methotrexate Injection can be given to you:

- through an intravenous (IV) line in your vein

- by injection into a large muscle (intramuscular injection)

- injected under your skin (subcutaneous injection)

- for certain diseases the preservative-free formulation of Methotrexate Injection can also be injected through your spine directly into your spinal fluid.

If you are receiving Methotrexate Injection to treat your cancer:

- Your healthcare provider will decide your dose, how you will receive Methotrexate Injection, and how often you need to receive it, depending on your medical condition that is being treated.
- If you are receiving high-dose Methotrexate Injection to treat your cancer, you will receive the medicine leucovorin to help prevent severe side effects ("rescue") to your bone marrow and other normal cells in your body. You will also receive intravenous (IV) fluids and other medicines to help prevent and treat side effects.
- If you are receiving a "moderate-dose" of Methotrexate Injection to treat your cancer, you may also receive leucovorin.
- Do not take folic acid or folinic acid during treatment with Methotrexate Injection to treat your cancer, unless your healthcare provider tells you to. Taking folic acid or folinic acid with Methotrexate Injection may make your treatment less effective.
- Your healthcare provider will do blood tests to check for side effects during treatment with Methotrexate Injection.
- Your healthcare provider may stop your treatment, change when you receive your treatment, or change the dose of your treatment if you have certain side effects while receiving Methotrexate Injection.

If you are receiving Methotrexate Injection for treatment of severe psoriasis, rheumatoid arthritis, or polyarticular juvenile idiopathic arthritis:

- You should receive your Methotrexate Injection dose 1 time each week, not every day. Serious side effects and death have happened in people who mistakenly have taken Methotrexate Injection every day instead of 1 time each week.
- Take folic acid or folinic acid every day during treatment with Methotrexate Injection, as instructed by your healthcare provider, to help reduce the chance of developing certain side effects, such as mouth sores.
- If you receive too much Methotrexate Injection call your healthcare provider or go to your nearest hospital emergency room right way. You will need to receive a medicine as soon as possible to help reduce side effects that could be severe and could cause death.

In all patients receiving Methotrexate Injection:

- If you miss receiving a dose of Methotrexate Injection, call your healthcare provider for instructions about when to receive your next dose of Methotrexate Injection.

What are the possible side effects of Methotrexate Injection?
Methotrexate Injection can cause serious side effects, including:

- See “What is the most important information I should know about Methotrexate Injection?”
- Tumor lysis syndrome (TLS). TLS is caused by the fast breakdown of cancer cells. TLS can cause kidney failure and the need for dialysis treatment, abnormal heart rhythm, seizure, and sometimes death. Your healthcare provider may do blood tests to check you for TLS if you are receiving Methotrexate Injection as a cancer treatment. Your healthcare provider will treat you as needed to prevent or manage TLS if you develop it during treatment with Methotrexate Injection.
- New (secondary) cancers. New (secondary) cancers can happen in people who take or receive Methotrexate Injection at any dose.
  - Certain blood cancers can happen during treatment with low-dose Methotrexate Injection. In some cases, these blood cancers may completely go away (regress completely) after Methotrexate Injection is stopped.
  - If you develop one of these blood cancers during treatment with Methotrexate Injection, your healthcare provider will stop your treatment, and treat as needed if the new cancer does not go away after Methotrexate Injection is stopped.
- Increased risk of soft tissue and bone problems due to receiving Methotrexate Injection in combination with radiation therapy. In people who receive Methotrexate Injection, some soft tissue in your body may die and some bone cells may die. People who receive radiation therapy in combination with Methotrexate Injection have an increased risk of this happening.

The most common side effects of Methotrexate Injection include:

- mouth sores or ulcers
- nausea
- decreased white blood cell count. See “What is the most important information I should know about Methotrexate Injection?”
- upset stomach

Possible fertility problems (infertility) in males and females. Methotrexate Injection can cause fertility problems in males and females, and cause sperm production to stop in males, and menstrual problems in females. In females, your periods (menstrual cycle) may be irregular or completely stop when you receive Methotrexate Injection. Your periods may or may not return to normal following treatment. It is not known if your fertility will return after treatment. Talk to your healthcare provider about your risk for infertility if this is a concern for you.
These are not all of the possible side effects of Methotrexate Injection.

Call your doctor for medical advice about side effects. You may report side effects to FDA at 1-800-FDA-1088.

General information about the safe and effective use of Methotrexate Injection.
Medicines are sometimes prescribed for purposes other than those listed in a Patient Information leaflet.
You can ask your pharmacist or healthcare provider for information about Methotrexate Injection that is written for health professionals.

What are the ingredients in Methotrexate Injection?
Active ingredient: methotrexate.
Inactive ingredients for Methotrexate Injection Preservative-free: sodium chloride. May contain sodium hydroxide and/or hydrochloric acid to adjust pH to 8.5.
Inactive ingredients for Methotrexate Injection with Preservative: benzyl alcohol and sodium chloride. May contain sodium hydroxide and/or hydrochloric acid to adjust pH to 8.5.
Distributed by Hospira, Inc., Lake Forest, IL 60045

Novaplus is a registered trademark of Vizient, Inc.
LAB-1476-2.0
For more information, go to www.pfizer.com or call 1-800-438-1985.

This Patient Information has been approved by the U.S. Food and Drug Administration. Issued: 05/2025

PRINCIPAL DISPLAY PANEL - 2 mL Vial Label

Sterile
NDC 61703-350-09
2 mL Multiple-dose Vial

Methotrexate
Injection, USP
Rx only

50 mg/2 mL (25 mg/mL)

Isotonic Liquid

Contains preservative Hazardous Drug

PRINCIPAL DISPLAY PANEL - 2 mL Vial Carton

VIAL

5 x 2 mL Multiple-dose Vial
NDC 61703-350-10

Sterile
Rx only

Methotrexate Injection, USP
50 mg/2 mL (25 mg/mL)

Isotonic Liquid

For Intravenous,
Intramuscular and
Subcutaneous Use Only

CONTAINS PRESERVATIVE
NOT FOR INTRATHECAL USE

novaplus™

Hazardous Drug

PRINCIPAL DISPLAY PANEL - 40 mL Vial Label

Sterile
NDC 61703-408-25

40 mL Single dose vial. Discard unused portion.
Rx only

Methotrexate
Injection, USP

1 g/40 mL (25 mg/mL)

Preservative Free

For Intravenous, Intramuscular,

Subcutaneous and Intrathecal Use Only

Hazardous Drug

novaplus™

PRINCIPAL DISPLAY PANEL - 40 mL Vial Carton

VIAL

1 x 40 mL Vial
NDC 61703-408-25

Sterile
Rx only

Methotrexate
Injection, USP

1 g/40 mL (25 mg/mL)

Preservative Free

For Intravenous, Intramuscular,

Subcutaneous and Intrathecal Use Only

Single dose vial. Discard unused portion.

Hazardous Drug